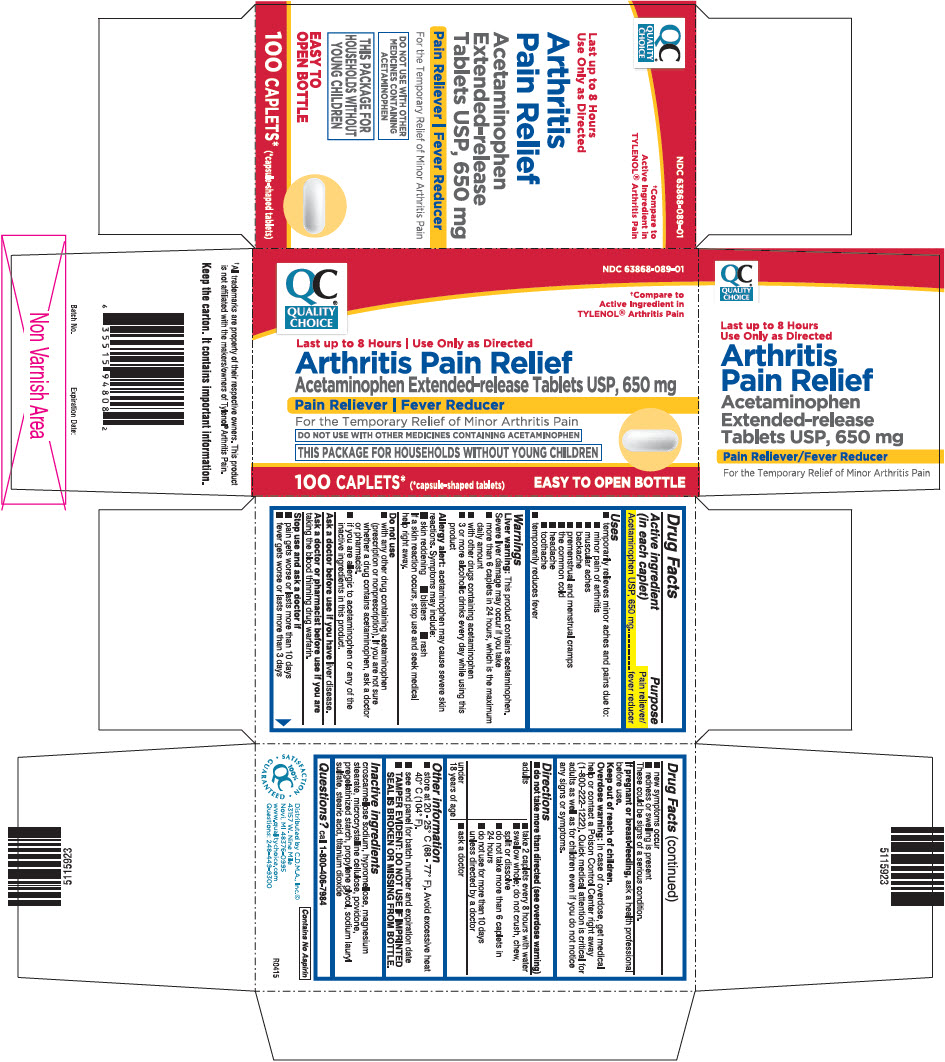 DRUG LABEL: Acetaminophen
NDC: 63868-089 | Form: TABLET, FILM COATED, EXTENDED RELEASE
Manufacturer: Chain Drug Marketing Association Inc.
Category: otc | Type: HUMAN OTC DRUG LABEL
Date: 20241227

ACTIVE INGREDIENTS: ACETAMINOPHEN 650 mg/1 1
INACTIVE INGREDIENTS: CROSCARMELLOSE SODIUM; HYPROMELLOSE, UNSPECIFIED; MAGNESIUM STEARATE; MICROCRYSTALLINE CELLULOSE; POVIDONE, UNSPECIFIED; STARCH, CORN; PROPYLENE GLYCOL; SODIUM LAURYL SULFATE; STEARIC ACID; TITANIUM DIOXIDE

Acetaminophen

Drug Facts

Active ingredient (in each caplet)

Acetaminophen USP, 650 mg

Purpose

Pain reliever/fever reducer

Uses

- temporarily relieves minor aches and pains due to:
  - minor pain of arthritis
  - muscular aches
  - backache
  - premenstrual and menstrual cramps
  - the common cold
  - headache
  - toothache
- temporarily reduces fever

Warnings

Liver warning

This product contains acetaminophen. Severe liver damage may occur if you take

- more than 6 caplets in 24 hours, which is the maximum daily amount
- with other drugs containing acetaminophen
- 3 or more alcoholic drinks every day while using this product

Allergy alert:acetaminophen may cause severe skin reactions. Symptoms may include:

- skin reddening
- blisters
- rash

If a skin reaction occurs, stop use and seek medical help right away.

Do not use

- with any other drug containing acetaminophen (prescription or nonprescription). If you are not sure whether a drug contains acetaminophen, ask a doctor or pharmacist.
- if you are allergic to acetaminophen or any of the inactive ingredients in this product.

Ask a doctor before use if you haveliver disease.

Ask a doctor or pharmacist before use if you aretaking the blood thinning drug warfarin.

Stop use and ask a doctor if

- pain gets worse or lasts more than 10 days
- fever gets worse or lasts more than 3 days
- new symptoms occur
- redness or swelling is present

These could be signs of a serious condition.

PREGNANCY OR BREAST FEEDING

If pregnant or breast-feeding,ask a health professional before use.

Keep out of reach of children.

Overdose warning

In case of overdose, get medical help or contact a Poison Control Center right away (1-800-222-1222). Quick medical attention is critical for adults as well as for children even if you do not notice any signs or symptoms.

Directions

- do not take more than directed (see overdose warning)

adults | - take 2 caplets every 8 hours with water - swallow whole; do not crush, chew, split or dissolve - do not take more than 6 caplets in 24 hours - do not use for more than 10 days unless directed by a doctor
under 18 years of age | - ask a doctor

Other information

- store at 20 - 25° C (68 - 77° F). Avoid excessive heat 40° C (104° F).
- see end panel for batch number and expiration date
- TAMPER EVIDENT: DO NOT USE IF IMPRINTED SEAL IS BROKEN OR MISSING FROM BOTTLE.

Inactive ingredients

croscarmellose sodium, hypromellose, magnesium stearate, microcrystalline cellulose, povidone, pregelatinized starch, propylene glycol, sodium lauryl sulfate, stearic acid, titanium dioxide

Questions?

call 1-800-406-7984

Distributed by C.D.M.A., Inc.©
43157 W. Nine Mile
Novi, MI 48376-0995

PRINCIPAL DISPLAY PANEL - 100 Caplet Bottle Carton

QC®
QUALITY
CHOICE

NDC 63868-089-01

†Compare to
Active Ingredient in
TYLENOL®Arthritis Pain

Last up to 8 Hours | Use Only as Directed

Arthritis Pain Relief

Acetaminophen Extended-release Tablets USP, 650 mg

Pain Reliever | Fever Reducer

For the Temporary Relief of Minor Arthritis Pain

DO NOT USE WITH OTHER MEDICINES CONTAINING ACETAMINOPHEN

THIS PACKAGE FOR HOUSEHOLDS WITHOUT YOUNG CHILDREN

100 CAPLETS*
(*capsule-shaped tablets)

EASY TO OPEN BOTTLE